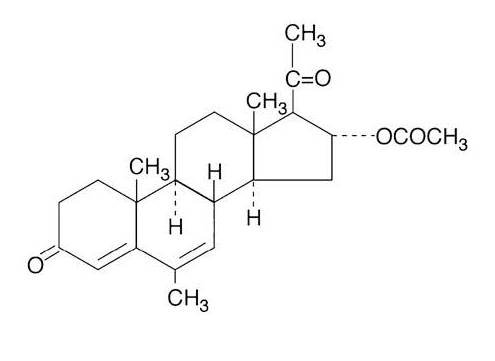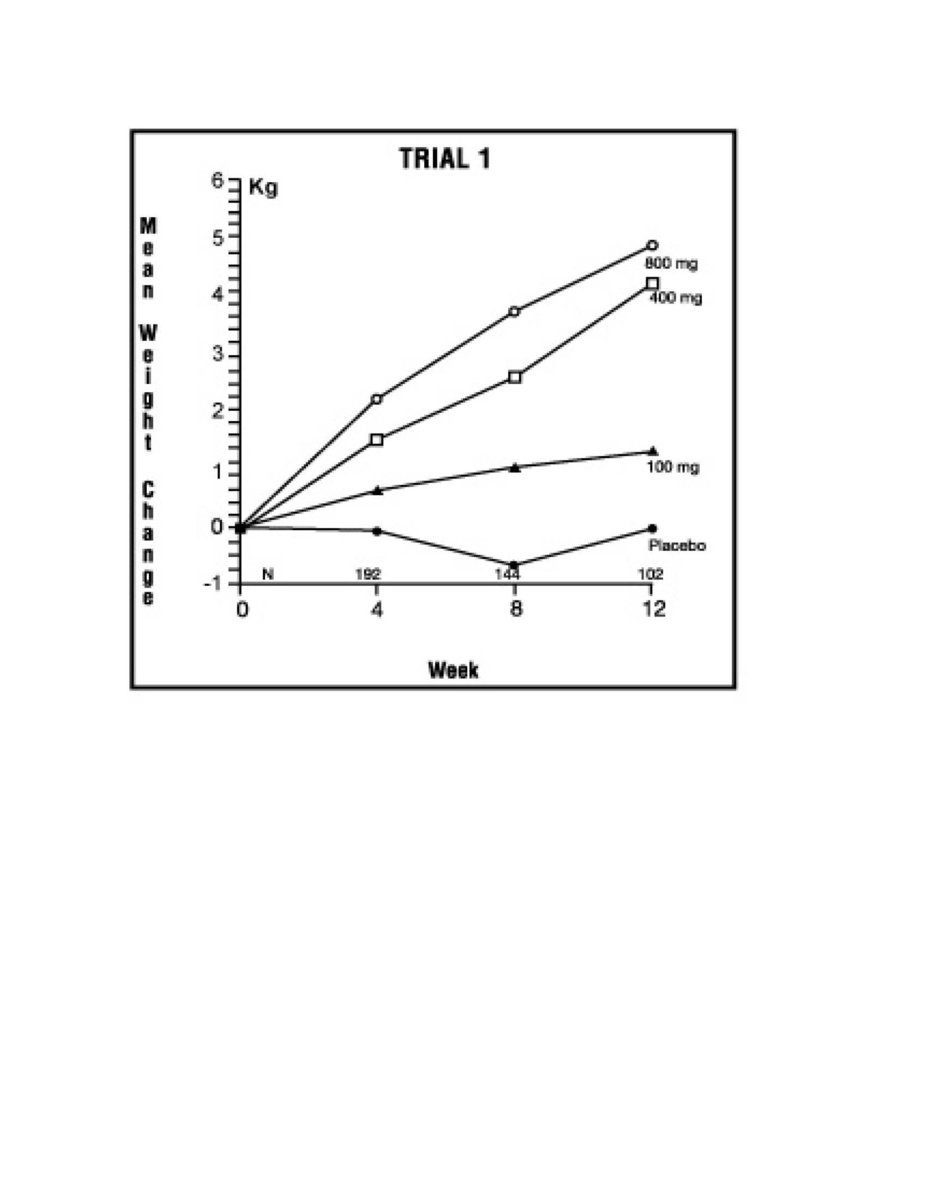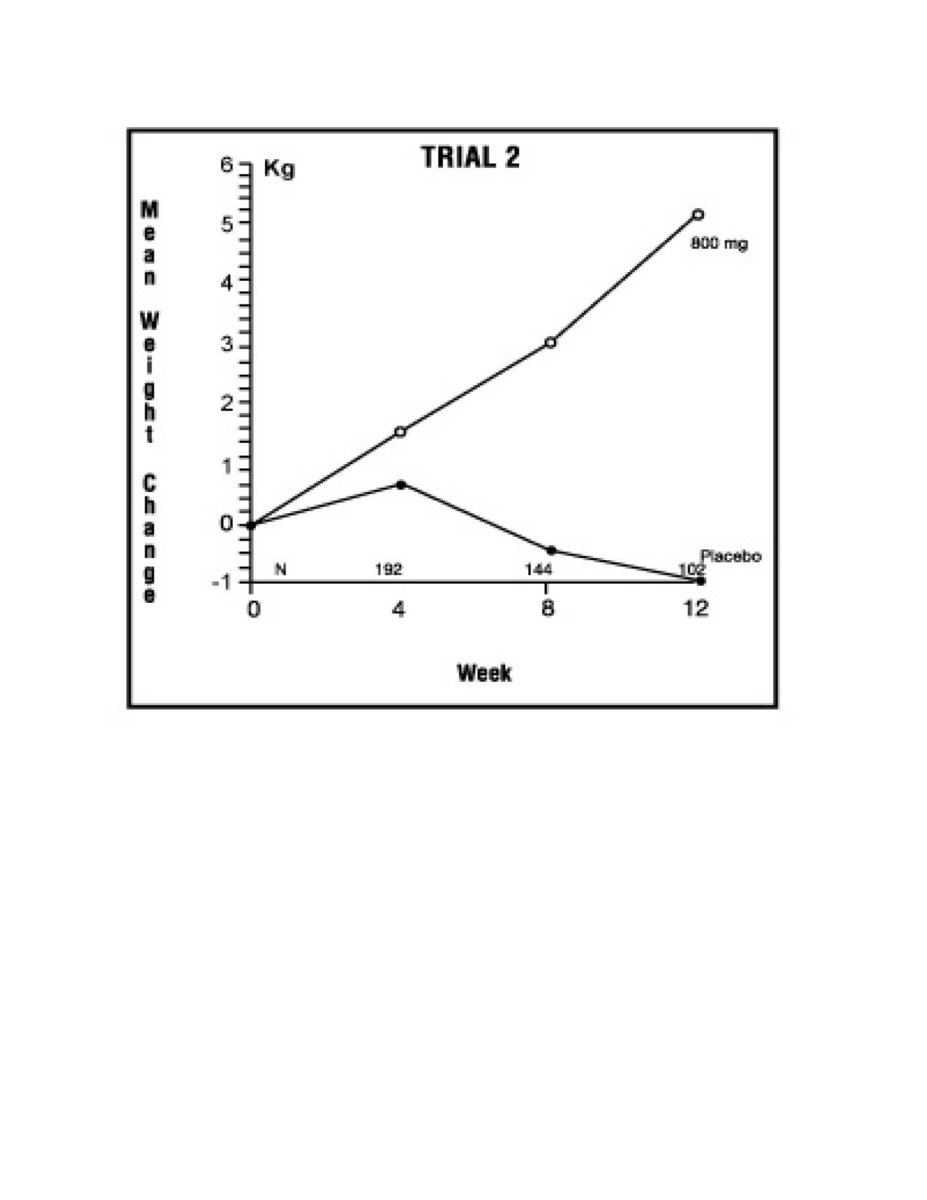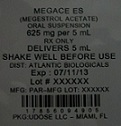 DRUG LABEL: Megace ES
NDC: 17856-0949 | Form: SUSPENSION
Manufacturer: Atlantic Biologicals Corps
Category: prescription | Type: HUMAN PRESCRIPTION DRUG LABEL
Date: 20140318

ACTIVE INGREDIENTS: MEGESTROL ACETATE 125 mg/1 mL
INACTIVE INGREDIENTS: CITRIC ACID MONOHYDRATE; DOCUSATE SODIUM; SODIUM BENZOATE; TRISODIUM CITRATE DIHYDRATE; SUCROSE; LEMON; LIME (CITRUS); HYPROMELLOSE 2208 (100 MPA.S); WATER

HIGHLIGHTS OF PRESCRIBING INFORMATION

These highlights do not include all the information needed to use Megace ES safely and effectively. See full prescribing information for Megace ES. Megace ES (megestrol acetate, USP) Oral Suspension Initial U.S. Approval: 1993®®
®

1 INDICATIONS AND USAGE

Megace ES oral suspension is a progestin indicated for the treatment of anorexia, cachexia, or an unexplained significant weight loss in patients with a diagnosis of acquired immunodeficiency syndrome (AIDS) .® (1)

2 DOSAGE AND ADMINISTRATION

The recommended adult initial dosage of Megace ES oral suspension is 625 mg/day (5 mL/day or one teaspoon daily). Shake the container well before using .® (2)

3 DOSAGE FORMS AND STRENGTHS

Oral suspension containing 125 mg of megestrol acetate per mL . (3)

4 CONTRAINDICATIONS

- History of hypersensitivity to megestrol acetate or any component of the formulation . (4.1)
- Known or suspected pregnancy . (4.2) (8.1)

5 WARNINGS AND PRECAUTIONS

- Women of childbearing potential should be advised to avoid becoming pregnant . (5.2)
- Use with caution in patients with a history of thromboembolic disease . (5.1)
- Clinical cases of overt Cushing's Syndrome have been reported in association with the chronic use of megestrol acetate. In addition, clinical cases of adrenal insufficiency have been observed in patients receiving or being withdrawn from chronic megestrol acetate in the stressed and non-stressed state . (5.3)
- New onset and exacerbation of pre-existing diabetes have been reported . (5.4)

6 ADVERSE REACTIONS

The most common adverse events occurring in > 5% of all patients receiving 800mg/20mL of megestrol acetate oral suspension in the two clinical efficacy trials were nausea, diarrhea, impotence, rash, flatulence, hypertension, and asthenia . (6.2)

To report SUSPECTED ADVERSE REACTIONS, contact Par Pharmaceutical, Inc. at 1-800-828-9393, option 3 or FDA at 1-800-FDA-1088 or www.fda.gov/medwatch.

7 DRUG INTERACTIONS

Due to a significant decrease in indinavir exposure, administration of a higher dose of indinavir should be considered when coadministering with megestrol acetate (,). 7.112.3

8 USE IN SPECIFIC POPULATIONS

- : In general, dose selection for an elderly patient should be cautious, usually starting at the low end of the dosing range, reflecting the greater frequency of decreased hepatic, renal or cardiac function, and of concomitant disease or other therapy . Geriatrics (8.5)
- : Because of the potential for adverse effects on the newborn, nursing should be discontinued if Megace ES oral suspension is required (8.3). Nursing Mothers®

FULL PRESCRIBING INFORMATION

1 INDICATIONS AND USAGE

Megace ES oral suspension is indicated for the treatment of anorexia, cachexia, or an unexplained significant weight loss in patients with a diagnosis of acquired immunodeficiency syndrome (AIDS). ®

1.1 Limitations of Use

Other Treatable Causes

Therapy with megestrol acetate for weight loss should only be instituted after treatable causes of weight loss are sought and addressed. These treatable causes include possible malignancies, systemic infections, gastrointestinal disorders affecting absorption, endocrine disease, renal disease or psychiatric diseases.

Prophylactic Use

Megestrol acetate is not intended for prophylactic use to avoid weight loss.

2 DOSAGE AND ADMINISTRATION

The recommended adult initial dosage of Megace ES oral suspension is 625 mg/day (5 mL/day or one teaspoon daily). Shake the container well before using.®

This strength (125 mg/mL) is not substitutable with other strengths (e.g., 40 mg/mL). Refer to the prescribing information of the 40 mg/mL product for dosage recommendations for the 40 mg/mL strength.

3 DOSAGE FORMS AND STRENGTHS

Megace ES is a milky white, lemon-lime flavored oral suspension containing 125 mg of megestrol acetate per mL. Megace ES does not contain the same amount of megestrol acetate as Megace oral suspension or any of the other megestrol acetate oral suspensions®®® (2).

4 CONTRAINDICATIONS

4.1 Hypersensitivity Reaction

History of hypersensitivity to megestrol acetate or any component of the formulation.

4.2 Pregnancy

Known or suspected pregnancy.

5 WARNINGS AND PRECAUTIONS

5.1 General

- Effects on HIV viral replication have not been determined.
- Use with caution in patients with a history of thromboembolic disease.

5.2 Fetal Effects

Megestrol acetate may cause fetal harm when administered to a pregnant woman. For animal data on fetal effects, see There are no adequate and well-controlled studies in pregnant women. If this drug is used during pregnancy, or if the patient becomes pregnant while taking (receiving) this drug, the patient should be apprised of the potential hazard to the fetus. Women of childbearing potential should be advised to avoid becoming pregnant. NonClinical Toxicology: Impairment of Fertility (13.1).

5.3 Adrenal Insufficiency

The glucocorticoid activity of megestrol acetate oral suspension has not been fully evaluated. Clinical cases of overt Cushing's Syndrome have been reported in association with the chronic use of megestrol acetate. In addition, clinical cases of adrenal insufficiency have been observed in patients receiving or being withdrawn from chronic megestrol acetate therapy in the stressed and non-stressed state. Furthermore, adrenocorticotropin (ACTH) stimulation testing has revealed the frequent occurrence of asymptomatic pituitary-adrenal suppression in patients treated with chronic megestrol acetate therapy. Therefore, the possibility of adrenal insufficiency should be considered in any patient receiving or being withdrawn from chronic Megace ES therapy who presents with symptoms and/or signs suggestive of hypoadrenalism (e.g., hypotension, nausea, vomiting, dizziness, or weakness) in either the stressed or non-stressed state. Laboratory evaluation for adrenal insufficiency and consideration of replacement or stress doses of a rapidly acting glucocorticoid are strongly recommended in such patients. Failure to recognize inhibition of the hypothalamic-pituitary adrenal axis may result in death. Finally, in patients who are receiving or being withdrawn from chronic Megace ES therapy, consideration should be given to the use of empiric therapy with stress doses of a rapidly acting glucocorticoid during stress or serious intercurrent illness (e.g., surgery, infection). ®®

5.4 Diabetics

Clinical cases of new onset diabetes mellitus and exacerbation of pre-existing diabetes mellitus have been reported in association with the chronic use of megestrol acetate.

6 ADVERSE REACTIONS

6.1 Serious and Otherwise Important Adverse Reactions

The following serious reactions and otherwise important adverse drug reactions are discussed in greater detail in other sections of the labeling:
- Hypersensitivity [see Contraindications (4.1)]
- Pregnancy [see Contraindications (4.2)]
- Fetal Effects [see Warnings and Precautions (5.2)]
- Thromboembolic Disease [see Warnings and Precautions (5.1)]
- Adrenal Insufficiency [see Warnings and Precautions (5.3)]

6.2 Clinical Trial Experience

Because clinical trials are conducted under widely varying conditions, adverse reactions observed in the clinical trials of a drug cannot be directly compared to rates in the clinical trials of another drug and may not reflect the rates observed in practice.

The safety of Megace ES (megestrol acetate oral suspension, 125 mg/mL) was based on three studies of megestrol acetate oral suspension (40 mg/mL). The adverse reaction profile of these 3 studies are presented below.®

Adverse events which occurred in at least 5% of patients in any arm of the two clinical efficacy trials and the open trial for megestrol acetate oral suspension are listed below by treatment group. All patients listed had at least one post baseline visit during the 12 study weeks.

Table 1: Adverse Events
Percentage of Patients Reporting Adverse Events
 | Trial 1; (N=236) |  |  |  | Trial 2; (N=87) |  | Open Label; Trial
 | Placebo |  |  |  | Placebo
Megestrol; Acetate mg/day | 0 | 100 | 400 | 800 | 0 | 800 | 1200
No. of Patients | N=34 | N=68 | N=69 | N=65 | N=38 | N=49 | N=176
Diarrhea | 15 | 13 | 8 | 15 | 8 | 6 | 10
Impotence | 3 | 4 | 6 | 14 | 0 | 4 | 7
Rash | 9 | 9 | 4 | 12 | 3 | 2 | 6
Flatulence | 9 | 0 | 1 | 9 | 3 | 10 | 6
Hypertension | 0 | 0 | 0 | 8 | 0 | 0 | 4
Asthenia | 3 | 2 | 3 | 6 | 8 | 4 | 5
Insomnia | 0 | 3 | 4 | 6 | 0 | 0 | 1
Nausea | 9 | 4 | 0 | 5 | 3 | 4 | 5
Anemia | 6 | 3 | 3 | 5 | 0 | 0 | 0
Fever | 3 | 6 | 4 | 5 | 3 | 2 | 1
Libido; Decreased | 3 | 4 | 0 | 5 | 0 | 2 | 1
Dyspepsia | 0 | 0 | 3 | 3 | 5 | 4 | 2
Hyperglycemia | 3 | 0 | 6 | 3 | 0 | 0 | 3
Headache | 6 | 10 | 1 | 3 | 3 | 0 | 3
Pain | 6 | 0 | 0 | 2 | 5 | 6 | 4
Vomiting | 9 | 3 | 0 | 2 | 3 | 6 | 4
Pneumonia | 6 | 2 | 0 | 2 | 3 | 0 | 1
Urinary Frequency | 0 | 0 | 1 | 2 | 5 | 2 | 1

Adverse events which occurred in 1% to 3% of all patients enrolled in the two clinical efficacy trials with at least one follow-up visit during the first 12 weeks of the study are listed below by body system. Adverse events occurring less than 1% are not included. There were no significant differences between incidence of these events in patients treated with megestrol acetate and patients treated with placebo.

abdominal pain, chest pain, infection, moniliasis and sarcoma Body as a Whole -

cardiomyopathy and palpitation Cardiovascular System -

constipation, dry mouth, hepatomegaly, increased salivation and oral moniliasis Digestive System -

leukopenia Hemic and Lymphatic System -

LDH increased, edema and peripheral edema Metabolic and Nutritional -

paresthesia, confusion, convulsion, depression, neuropathy, hypesthesia and abnormal thinking Nervous System -

dyspnea, cough, pharyngitis and lung disorder Respiratory System -

alopecia, herpes, pruritus, vesiculobullous rash, sweating and skin disorder Skin and Appendages -

amblyopia Special Senses -

albuminuria, urinary incontinence, urinary tract infection and gynecomastia. Urogenital System -

6.3 Postmarketing Experience

Postmarketing reports associated with megestrol acetate oral suspension include thromboembolic phenomena including thrombophlebitis, deep vein thrombosis, and pulmonary embolism; and glucose intolerance [see Warnings and Precautions (5.1,5.4)].

7 DRUG INTERACTIONS

7.1 Indinavir

Due to the significant decrease in the exposure of indinavir by megestrol acetate, administration of a higher dose of indinavir should be considered when coadministering with megestrol acetate . [See Clinical Pharmacology (12.3)]

7.2 Zidovudine and Rifabutin

No dosage adjustment for zidovudine and rifabutin is needed when megestrol acetate is coadministered with these drugs . [See Clinical Pharmacology (12.3)]

8 USE IN SPECIFIC POPULATIONS

8.1 Pregnancy

Pregnancy Category X No adequate animal teratology information is available at clinically relevant doses. Pregnant rats treated with low doses of megestrol acetate (0.02-fold the recommended clinical dose) resulted in a reduction in fetal weight and number of live births, and feminization of male fetuses. [see Warnings and Precautions (5.2)].

8.3 Nursing Mothers

Because of the potential for adverse effects on the newborn, nursing should be discontinued if Megace ES oral suspension is required. ®

8.4 Pediatric Use

Safety and effectiveness in pediatric patients have not been established.

8.5 Geriatric Use

Clinical studies of megestrol acetate oral suspension in the treatment of anorexia, cachexia, or an unexplained significant weight loss in patients with AIDS did not include sufficient numbers of patients aged 65 years and older to determine whether they respond differently than younger patients. Other reported clinical experience has not identified differences in responses between elderly and younger patients. In general, dose selection for an elderly patient should be cautious, usually starting at the low end of the dosing range, reflecting the greater frequency of decreased hepatic, renal, or cardiac function, and of concomitant disease or other drug therapy.

Megestrol acetate is known to be substantially excreted by the kidney, and the risk of toxic reactions to this drug may be greater in patients with impaired renal function. Because elderly patients are more likely to have decreased renal function, care should be taken in dose selection, and it may be useful to monitor renal function.

8.6 Use in Women

Megestrol acetate has had limited use in HIV infected women.

All 10 women in the clinical trials reported breakthrough bleeding. Megace ES is a progesterone derivative, which may induce vaginal bleeding in women.®

10 OVERDOSAGE

No serious unexpected side effects have resulted from studies involving megestrol acetate oral suspension administered in dosages as high as 1200 mg/day. In post-marketing experience, limited reports of overdose have been received. Signs and symptoms reported in the context of overdose included diarrhea, nausea, abdominal pain, shortness of breath, cough, unsteady gait, listlessness, and chest pain. There is no specific antidote for overdose with Megace ES oral suspension. In case of overdose, appropriate supportive measures should be taken. Megestrol acetate has not been tested for dialyzability; however, due to its low solubility it is postulated that dialysis would not be an effective means of treating overdose. ®

11 DESCRIPTION

Megace ES oral suspension contains megestrol acetate, a synthetic derivative of the naturally occurring steroid hormone, progesterone. Megestrol acetate is a white, crystalline solid chemically designated as 17-Hydroxy-6-methyl pregna-4,6-diene-3,20-dione acetate. Solubility at 37° C in water is 2 mcg per mL, solubility in plasma is 24 mcg per mL. Its molecular weight is 384.52. ®
The chemical formula is C H O and the structural formula is represented as follows: 24324

Figure 1: Megestrol Acetate Chemical Structure

Megace ES is an oral suspension containing 125 mg of megestrol acetate per mL.®

Megace ES oral suspension contains the following inactive ingredients: alcohol (max 0.06% v/v from flavor), artificial lime flavor, citric acid monohydrate, docusate sodium, hydroxypropyl methylcellulose (hypromellose), natural and artificial lemon flavor, purified water, sodium benzoate, sodium citrate dihydrate, and sucrose.®

12 CLINICAL PHARMACOLOGY

12.1 Mechanism of Action

Several investigators have reported on the appetite enhancing property of megestrol acetate and its possible use in cachexia. The precise mechanism by which megestrol acetate produces effects in anorexia and cachexia is unknown at the present time.

12.3 Pharmacokinetics

Absorption and Distribution

Mean plasma concentrations of megestrol acetate after administration of 625 mg (125 mg/mL) of Megace ES oral suspension are equivalent under fed conditions to 800 mg (40 mg/mL) of megestrol acetate oral suspension in healthy volunteers. ®
In order to characterize the dose proportionality of Megace ES, pharmacokinetic studies across a range of doses were conducted when administered under fasting and fed conditions. Pharmacokinetics of megestrol acetate was linear in the dosing range between 150 mg and 675 mg after Megace ES administration regardless of meal condition. The mean peak plasma concentration (C) and the mean area under the concentration time-curve (AUC) after a high fat meal were increased by 48% and 36%, respectively, compared to those under the fasting condition after 625 mg Megace ES administration. This food effect is less than that seen for the original formulation, megestrol acetate 800 mg/20 mL, where a high fat meal significantly increased AUC and C of megestrol acetate to 2-fold and 7-fold, respectively, compared to those under the fasting condition. There was no difference in safety following administration in the fed state, therefore Megace ES could be taken without regard to meals. ®®max®max®
Plasma steady state pharmacokinetics of megestrol acetate was evaluated in 10 adult, cachectic male adult patients with acquired immunodeficiency syndrome (AIDS) and an involuntary weight loss greater than 10% of baseline who received single oral doses of 800 mg/day of megestrol acetate oral suspension for 21 days. The Mean (±1SD) C of megestrol acetate was 753 (±539) ng/mL. The mean AUC was 10476 (±7788) ng x hr/mL. Median T value was five hours. maxmax
In another study, 24 asymptomatic HIV seropositive male adult subjects were dosed once daily with 750 mg of megestrol acetate oral suspension for 14 days. Mean C and AUC values were 490 (±238) ng/mL and 6779 (±3048) hr x ng/mL, respectively. The median T value was three hours. The mean C value was 202 (±101) ng/mL. The mean % of fluctuation value was 107 (±40). maxmaxmin

Metabolism and Excretion

The major route of drug elimination in humans is urine. When radio-labeled megestrol acetate was administered to humans in doses of 4 to 90 mg, the urinary excretion within 10 days ranged from 56.5% to 78.4% (mean 66.4%) and fecal excretion ranged from 7.7% to 30.3% (mean 19.8%). The total recovered radioactivity varied between 83.1% and 94.7% (mean 86.2%).
Megestrol acetate metabolites which were identified in urine constituted 5% to 8% of the dose administered. Respiratory excretion as labeled carbon dioxide and fat storage may have accounted for at least part of the radioactivity not found in urine and feces.
The mean elimination half-life of megestrol ranged from 20 to 50 hours in healthy subjects.
Specific Populations
The pharmacokinetics of megestrol acetate has not been studied in specific population, for example, pediatric, renal impairment, and hepatic impairment.
Drug Interactions
The effects of indinavir, zidovudine or rifabutin on the pharmacokinetics of megestrol acetate were not studied.
Zidovudine
Pharmacokinetic studies show that there are no significant alterations in exposure of zidovudine when megestrol acetate is administered with this drug.
Rifabutin
Pharmacokinetic studies show that there are no significant alterations in exposure of rifabutin when megestrol acetate is administered with this drug.
Indinavir
A pharmacokinetic study in healthy male subjects demonstrated that coadministration of megestrol acetate (675 mg for 14 days) and indinavir (single dose 800 mg) results in a significant decrease in the pharmacokinetic parameters (~32% for C and ~21% for AUC) of indinavir. max

13 NONCLINICAL TOXICOLOGY

13.1 Carcinogenesis and Mutagenesis and Impairment of Fertility

Data on carcinogenesis were obtained from studies conducted in dogs, monkeys and rats treated with megestrol acetate at doses up to 0.01 to 0.1-fold the recommended clinical dose (13.3 mg/kg/day) based on body mass. No males were used in the dog and monkey studies. In female beagles, megestrol acetate (0.01, 0.1 or 0.25 mg/kg/day) administered for up to 7 years induced both benign and malignant tumors of the breast. In female monkeys, no tumors were found following 10 years of treatment with 0.01, 0.1 or 0.5 mg/kg/day megestrol acetate. Pituitary tumors were observed in female rats treated with 3.9 or 10 mg/kg/day of megestrol acetate for 2 years. The relationship of these tumors in rats and dogs to humans is unknown but should be considered in assessing the risk-to-benefit ratio when prescribing Megace ES oral suspension and in surveillance of patients on therapy. ®
Megestrol acetate induced unscheduled DNA synthesis in primary cultures of human hepatocytes, but not in rat hepatocytes. Megestrol administered to mice increased the frequency of sister chromatid exchange and chromosomal aberrations in bone marrow cells after single intraperitonial doses of 16.25 and 32.50 mg/kg. Perinatal/postnatal (segment III) toxicity studies were performed in rats at doses up to 0.02 -fold the recommended clinical dose (13.3 mg/kg/day) based on body mass. In these low dose studies, the reproductive capability of male offspring of megestrol acetate-treated females was impaired. Similar results were obtained in dogs. No toxicity data are currently available on male reproduction (spermatogenesis) [see Warnings and Precautions (5.2)].

13.2 Animal Pharmacology and/or Toxicology

Long-term treatment with Megace ES may increase the risk of respiratory infections. A trend toward increased frequency of respiratory infections, decreased lymphocyte counts and increased neutrophil counts was observed in a two-year chronic toxicity/carcinogenicity study of megestrol acetate conducted in rats. ®

14 CLINICAL STUDIES

The efficacy of Megace ES (megestrol acetate oral suspension, 125 mg/mL) was based on two trials of megestrol acetate oral suspension (40 mg/mL). These two trials are described below. ®

Trial 1

One was a multicenter, randomized, double-blind, placebo-controlled study comparing megestrol acetate (MA) at doses of 100 mg, 400 mg, and 800 mg per day versus placebo in AIDS patients with anorexia/cachexia and significant weight loss. Of the 270 patients entered on study, 195 met all inclusion/exclusion criteria, had at least two additional post baseline weight measurements over a 12 week period or had one post baseline weight measurement but dropped out for therapeutic failure. The percent of patients gaining 2.3 kg or more at maximum weight gain in 12 study weeks was statistically significantly greater for the 800 mg (64%) and 400 mg (57%) MA-treated groups than for the placebo group (24%). Mean weight increased from baseline to last evaluation in 12 study weeks in the 800 mg MA-treated group by 3.5 kg, the 400 mg MA group by 1.9 kg, the 100 mg MA group by 0.9 kg and decreased in the placebo group by 0.7 kg. Mean weight changes at 4, 8 and 12 weeks for patients evaluable for efficacy in the two clinical trials is shown graphically. Changes in body composition during the 12 study weeks as measured by bioelectrical impedance analysis showed increases in non-water body weight in the MA-treated groups. In addition, edema developed or worsened in only 3 patients.
Greater percentages of MA-treated patients in the 800 mg group (89%), the 400 mg group (68%) and the 100 mg group (72%), than in the placebo group (50%), showed an improvement in appetite at last evaluation during the 12 study weeks. A statistically significant difference was observed between the 800 mg MA-treated group and the placebo group in the change in caloric intake from baseline to time of maximum weight change. Patients were asked to assess weight change, appetite, appearance, and overall perception of well-being in a 9 question survey. At maximum weight change only the 800 mg MA-treated group gave responses that were statistically significantly more favorable to all questions when compared to the placebo-treated group. A dose response was noted in the survey with positive responses correlating with higher dose for all questions.

Trial 2

The second trial was a multicenter, randomized, double-blind, placebo-controlled study comparing megestrol acetate 800 mg/day versus placebo in AIDS patients with anorexia/cachexia and significant weight loss. Of the 100 patients entered on study, 65 met all inclusion/exclusion criteria, had at least two additional post baseline weight measurements over a 12 week period or had one post baseline weight measurement but dropped out for therapeutic failure. Patients in the 800 mg MA-treated group had a statistically significantly larger increase in mean maximum weight change than patients in the placebo group. From baseline to study week 12, mean weight increased by 5.1 kg in the MA-treated group and decreased 1.0 kg in the placebo group. Changes in body composition as measured by bioelectrical impedance analysis showed increases in non-water weight in the MA-treated group (see Clinical Studies table). No edema was reported in the MA-treated group. A greater percentage of MA-treated patients (67%) than placebo-treated patients (38%) showed an improvement in appetite at last evaluation during the 12 study weeks; this difference was statistically significant. There were no statistically significant differences between treatment groups in mean caloric change or in daily caloric intake at time to maximum weight change. In the same 9 question survey referenced in the first trial, patients' assessments of weight change, appetite, appearance, and overall perception of well-being showed increases in mean scores in MA-treated patients as compared to the placebo group.
In both trials, patients tolerated the drug well and no statistically significant differences were seen between the treatment groups with regard to laboratory abnormalities, new opportunistic infections, lymphocyte counts, T4 counts, T8 counts, or skin reactivity tests [see Adverse Reactions (6)].

Table 2: Megestrol Acetate Oral Suspension Clinical Efficacy Trials
Megestrol Acetate Oral Suspension Clinical Efficacy Trials
 | Trial 1; Study Accrual Dates; 11/88 to 12/90 |  |  |  | Trial 2; Study Accrual Dates; 5/89 to 4/91
Megestrol Acetate, mg/day | 0 | 100 | 400 | 800 | 0 | 800
Entered Patients | 38 | 82 | 75 | 75 | 48 | 52
Evaluable Patients | 28 | 61 | 53 | 53 | 29 | 36
Mean Change in Weight (kg)
Baseline to 12 Weeks | 0.0 | 1.3 | 4.2 | 4.9 | -1.0 | 5.1
% Patients ≥2.3 kg Gain at Last Evaluation in 12 Weeks | 21 | 44 | 57 | 64 | 28 | 47
Mean Changes in Body Composition*:
Fat Body Mass (kg) | 0.0 | 1.0 | 1.3 | 2.5 | 0.7 | 2.6
Lean Body Mass (kg) | -0.8 | -0.1 | 0.7 | 1.1 | -0.7 | -0.3
Water (liters) | -1.3 | -0.3 | 0.0 | 0.0 | -0.1 | -0.1
% Patients With Improved Appetite:
At Time of Maximum
Weight Change | 50 | 72 | 72 | 93 | 48 | 69
At Last Evaluation in 12 Weeks | 50 | 72 | 68 | 89 | 38 | 67
Mean Change in Daily Caloric Intake:
Baseline to Time of Maximum
Weight Change | -107 | 326 | 308 | 646 | 30 | 464
*Based on bioelectrical impedance analysis determinations at last evaluation in 12 weeks.

Figure 2: Mean Weight Change for Patients Evaluable for Efficacy in Trial 1

Figure 3: Mean Weight Change for Patients Evaluable for Efficacy in Trial 2

16 HOW SUPPLIED/STORAGE AND HANDLING

NDC:17856-0949-5 in a CUP of 5 SUSPENSIONS

16.1 How Supplied

Megace ES oral suspension is a milky white, lemon-lime flavored oral suspension containing 125 mg of megestrol acetate per mL. Available in bottles of 150 mL (5 fl oz) NDC 49884-949-69. ®

16.2 Storage

Store Megace ES oral suspension between 15° to 25° C (59° to 77° F) and dispense in a tight container. Protect from heat. ®

16.3 Safe Handling

Health Hazard Data

There is no threshold limit value established by OSHA, NIOSH, or ACGIH. Exposure or overdose at levels approaching recommended dosing levels could result in side effects described above Women at risk of pregnancy should avoid such exposure. [see Warnings and Precautions (5) and Adverse Reactions (6)].

17 PATIENT COUNSELING INFORMATION

The prescriber should inform the patient about the product differences to avoid overdosing or underdosing of megestrol acetate. The recommended adult dosage of Megace ES is one teaspoon (5 mL) once a day® [see table in Dosage and Administration (2)].
Patients using Megace ES should receive the following instructions: ®
- This medication is to be used as directed by the physician.
- Megace ES (625 mg/5 mL) does not contain the same amount of megestrol acetate as Megace oral suspension or any of the other megestrol acetate oral suspensions. Megace ES contains 625 mg of megestrol acetate per 5 mL (125mg/mL) whereas Megace oral suspension and other megestrol acetate oral suspensions contain 800 mg per 20 mL (40 mg/mL). ®®®®
- Report any adverse reaction experiences while taking this medication.
- Use contraception while taking this medication if you are a woman capable of becoming pregnant.
- Notify your physician if you become pregnant while taking this medication.

Manufactured by:

PAR PHARMACEUTICAL COMPANIES, INC.

Spring Valley, New York 10977

U.S. Patent No.:

6,592,903
7,101,576

Revised: 03/14 OS949-01-1-09

Megace® is a registered trademark of Bristol-Myers Squibb Company licensed to Par Pharmaceutical, Inc.